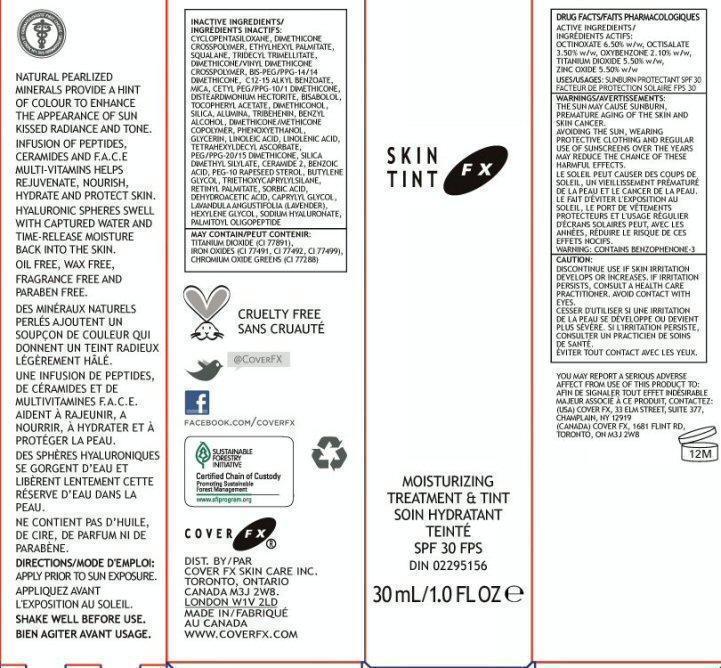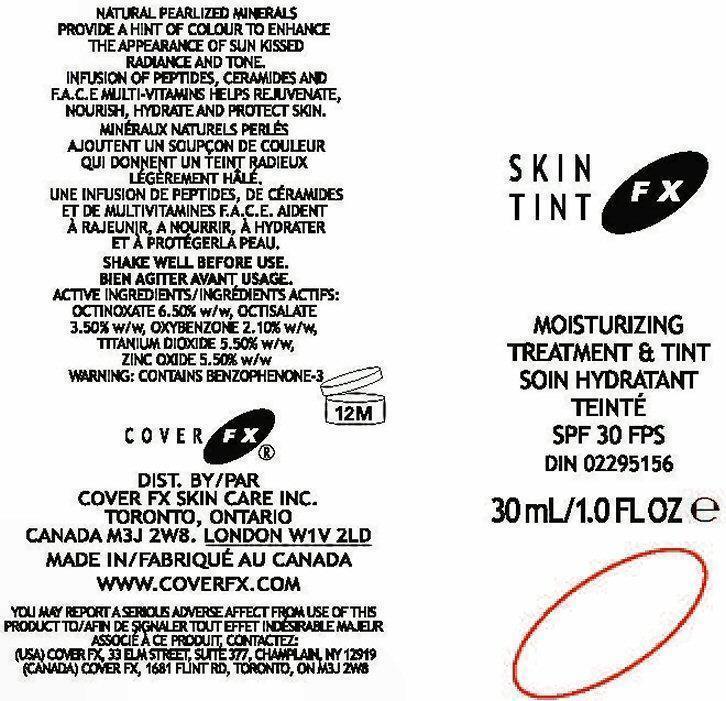 DRUG LABEL: Skin Tint FX
NDC: 68327-003 | Form: CREAM
Manufacturer: Cover FX Skin Care, Inc.
Category: otc | Type: HUMAN OTC DRUG LABEL
Date: 20130220

ACTIVE INGREDIENTS: OCTINOXATE 6.5 g/100 mL; OCTISALATE 3.5 g/100 mL; OXYBENZONE 2.1 g/100 mL; TITANIUM DIOXIDE 5.5 g/100 mL; ZINC OXIDE 5.5 g/100 mL
INACTIVE INGREDIENTS: CYCLOMETHICONE 5 ; DIMETHICONE/DIENE DIMETHICONE CROSSPOLYMER; ETHYLHEXYL PALMITATE; SQUALANE; TRIDECYL TRIMELLITATE; DIMETHICONE/VINYL DIMETHICONE CROSSPOLYMER (SOFT PARTICLE); ALKYL (C12-15) BENZOATE; MICA; CETYL PEG/PPG-10/1 DIMETHICONE (HLB 5); LEVOMENOL; .ALPHA.-TOCOPHEROL ACETATE; DIMETHICONOL (41 MPA.S); SILICON DIOXIDE; ALUMINUM OXIDE; TRIBEHENIN; BENZYL ALCOHOL; PHENOXYETHANOL; GLYCERIN; LINOLEIC ACID; LINOLENIC ACID; TETRAHEXYLDECYL ASCORBATE; PEG/PPG-20/15 DIMETHICONE; CERAMIDE 2; BENZOIC ACID; PEG-10 RAPESEED STEROL; BUTYLENE GLYCOL; TRIETHOXYCAPRYLYLSILANE; VITAMIN A PALMITATE; SORBIC ACID; DEHYDROACETIC ACID; CAPRYLYL GLYCOL; LAVENDER OIL; HEXYLENE GLYCOL; HYALURONATE SODIUM; PALMITOYL OLIGOPEPTIDE; TITANIUM DIOXIDE; FERRIC OXIDE RED; FERRIC OXIDE YELLOW; FERROSOFERRIC OXIDE; CHROMIC OXIDE; SILICA DIMETHYL SILYLATE

Active Ingredients

DRUG FACTS

ACTIVE INGREDIENTS:

OCTINOXATE 6.50% w/w, OCTISALATE 3.50% w/w, OXYBENZONE 2.10% w/w, TITANIUM DIOXIDE 5.50% w/w, ZINC OXIDE 5.50% w/w

Purpose

USES: SUNBURN PROTECTANT SPF 30

Use

SUNBURN PROTECTANT SPF 30

NATURAL PEARLIZED MINERALS PROVIDE A HINT OF COLOUR TO ENHANCE THE APPEARANCE OF SUN KISSED RADIANCE AND TONE.

INFUSION OF PEPTIDES, CERAMIDES, AND F.A.C.E MULTI-VITAMINS HELPS REJUVENATE, NOURISH, HYDRATE AND PROTECT SKIN. HYALURONIC SPHERES SWELL WITH CAPTURED WATER AND TIME-RELEASED MOISTURE BACK INTO THE SKIN.

Warnings

WARNINGS: THE SUN MAY CAUSE PREMATURE AGING OF THE SKIN AND SKIN CANCER.

AVOID THE SUN, WEARING PROTECTIVE CLOTHING AND REGULAR USE OF SUNSCREENS OVER THE YEARS MAY REDUCE THE CHANCE OF THESE HARMFUL EFFECTS.

WARNING: CONTAINS BENZOPHENONE-3

CAUTION:

DISCONTINUE USE IF SKIN IRRITATION DEVELOPS OR INCREASES. IF IRRITATION PERSISTS, CONSULT A HEALTH CARE PRACTITIONER. AVOID CONTACT WITH EYES.

You may report

YOUR MAY REPORT A SERIOUS ADVERSE AFFECT FROM THE USE OF THIS PRODUCT TO:

(USA) COVER FX, 33 ELM STREET, SUITE 377, CHAMPLAIN, NY 12919

Directions

APPLY PRIOR TO SUN EXPOSURE.

SHAKE WELL BEFORE USAGE

Inactive Ingredients

CYCLOPENTASILOXANE, DIMETHICONE CROSSPOLYMER, ETHYLHEXYL PALMITATE, SQUALANE, TRIDECYL TRIMELLITATE, DIMETHICONE /VINYL DIMETHICONE CROSSPOLYMER, BIS-PEG/PPG-14/14 DIMETHICONE, C 12-15 ALKYL BENZOATE, MICA, CETYL PEG/PPG-10/1 DIMETHICONE, DISTEARDIMONIUM HECTORITE, BISABOLOL, TOCOPHEYL ACETATE, DIMETHICONOL, SILIA, ALUMINA, TRIIBEHENIN, BENZYL ALCOHOL, DIMETHICONE/METHICONE COPOLYMER, PHENOXYETHANOL, GLYCERIN, LINOLEIC ACID, LINOLENIC ACID, TETRAHEXYLDECYL ASCORBATE, PEG/PPG-20/15 DIMETHICONE, SILICA, DIMETHYL SILYLATE, CERAMIDE-2, BENZOIC ACID, PEG-10 RAPESEED STEROL, BUTYLENE GLYCOL, TRIETHOXYCAPYLYSILANE, RETINYL PALMITATE, SORBIC ACID, DEHYDROACETIC ACID, CAPRYLYL GLYCOL, LAVANDULA ANGUSTIFOLIA (LAVENDER), HEXYLENE GLYCOL, SODIUM HYALURONATE, PALM OLIGOPEPTIDE

MAY CONTAIN:

TITANIUM OXIDE (CL 77891), IRON OXIDES (CL 77491), CL 77492, CL 77499), CHROMIUM OXIDE GREENS (CL 77288)

Package Label

SKIN TINT FX

MOISTURIZING TREATMENT AND TINT

SPF 30 FPS DIN 02295156 30Ml/1.0 fl oz

OIL FREE, WAX FREE, FRAGRANCE FREE, AND PARABEN FREE.

CRUELTY FREE

Cover Fx

FACEBOOK.COM/COVERFX SUSTAINABLE FORESTRY INITIATIVE Certified Chain of Custody Promoting Sustainable Forest Management www.sfprogram.org

COVER FX

DIST. BY COVER FX SKIN CARE INC. TORONTO, ONTARIO CANADA M3J 2W8. LONDON W1V 2LD MADE IN FABRIQUE AU CANADA

WWW.COVERFX.COM